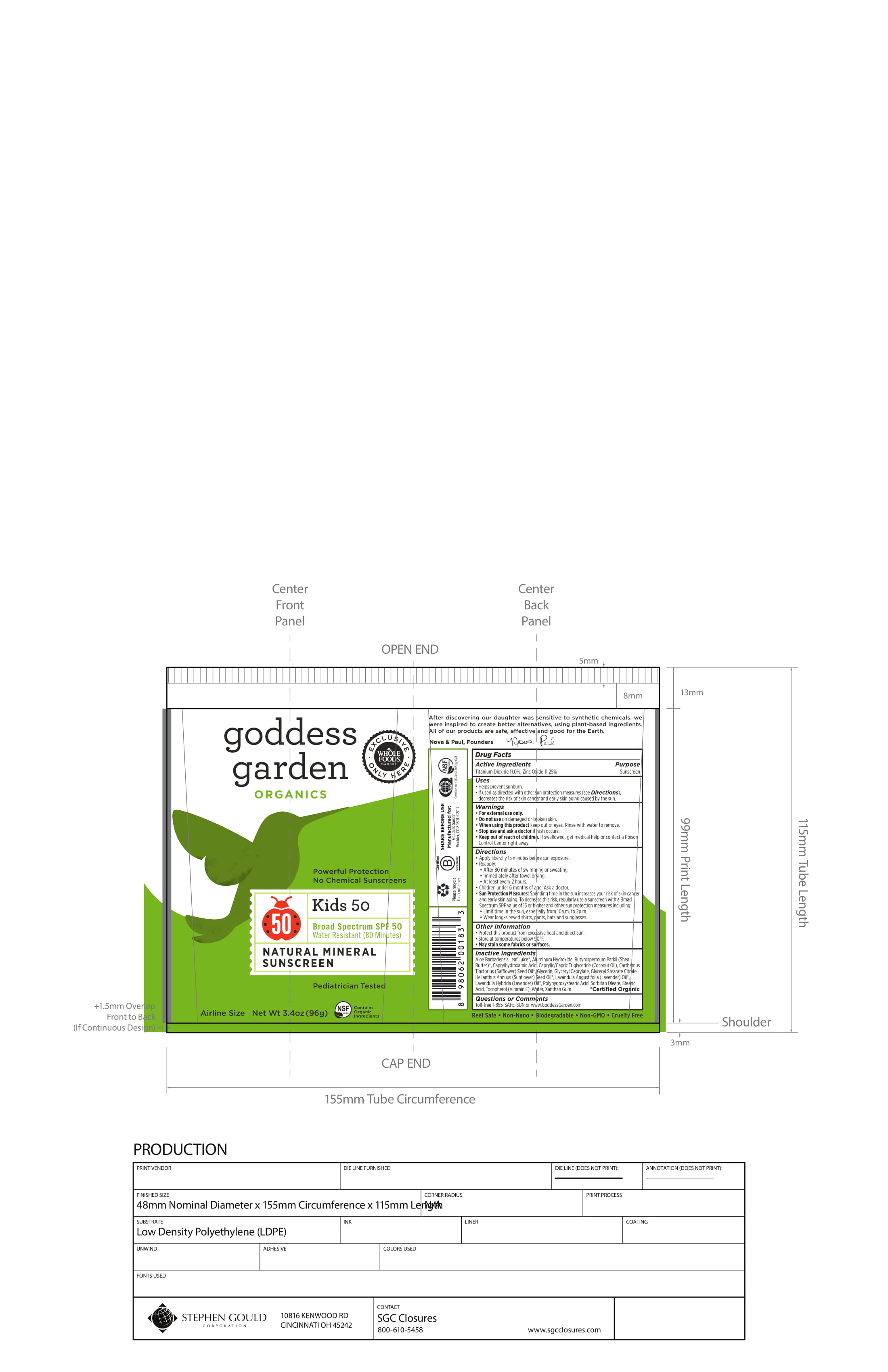 DRUG LABEL: Kids 50
NDC: 58479-206 | Form: LOTION
Manufacturer: Crossing cultures LLC dba Goddess Garden
Category: otc | Type: HUMAN OTC DRUG LABEL
Date: 20180417

ACTIVE INGREDIENTS: TITANIUM DIOXIDE 11 g/100 g; ZINC OXIDE 11.25 g/100 g
INACTIVE INGREDIENTS: CAPRYLHYDROXAMIC ACID; SAFFLOWER OIL; GLYCERIN; ALOE VERA LEAF; LAVENDER OIL; SORBITAN MONOOLEATE; TOCOPHEROL; WATER; GLYCERYL MONOCAPRYLATE; GLYCERYL STEARATE CITRATE; SUNFLOWER OIL; STEARIC ACID; XANTHAN GUM; ALUMINUM HYDROXIDE; SHEA BUTTER; MEDIUM-CHAIN TRIGLYCERIDES; LAVANDIN OIL; POLYHYDROXYSTEARIC ACID (2300 MW)

Goddess Garden Kids SPF50 Lotion

Active Ingredient

Titanium Dioxide 11.0%, Zinc Oxide 11.25%

Purpose

Sunscreen

Uses

* Helps prevent sunburn.

* If used as directed with other sun protection measures (see directions) decreases the risk of skin cancer and early skin aging caused by the sun.

Warnings

* For external use only.

* Do not use on damaged or broken skin.

* When using this product keep out of eyes. Rinse with water to remove.

* Stop use and ask a doctor if rash occurs.

* Keep out of reach of children. If swallowed, get medical help or contact a Poison Control Center right away.

Do not use

on damaged or broken skin

Stop use and ask doctor

if rash occurs

When using this product

keep out of eyes. Rinse with water and remove.

Keep out of reach of children

If swallowed, get medical help or contact Poison Center right away.

Directions

* Apply liberally 15 minutes before sun exposure.

* Reapply:

- After 80 minutes of swimming or sweating.

- Immediately after towel drying.

- At least every 2 hours.

* Children under 6 months of age: Ask a doctor.

* Sun Protection Measures: Spending time in the sun increases your risk of skin cancer and early skin aging. To decrease this risk, regularly use a sunscreen with a Broad Spectrum SPF value of 15 or higher and other sun protection measures including:

- Limit time in sun, especially from 10a.m. to 2p.m.

- Wear long-sleeved shirts, pants, hats and sunglasses.

Other Information

* Protect this product from excessive heat and direct sun.
* Store at temperatures below 90'F.
* May Stain some fabrics or surfaces.

Inactive Ingredients

Aloe Barbadensis Leaf Juice*, Aluminum Hydroxide, Butyrospermum Parkii (Shea Butter)*, Caprylhydroxamic Acid, Caprylic/Capric Triglyceride (Coconut Oil), Carthamus Tinctorius (Safflower) Seed Oil*, Glycerin, Glyceryl Caprylate, Glyceryl Stearate Citrate, Helianthus Annuus (Sunflower) Seed Oil*, Lavandula Angustifolia (Lavender) Oil*, Lavandula Hybrida (Lavender) Oil*, Polyhydroxystearic Acid, Sorbitan Oleate, Stearic Acid, Tocopherol (Vitamin E), Water, Xanthan Gum

* Certified Organic

Questions or Comments

Toll-free 1-855-SAFE-SUN or www.GoddessGarden.com